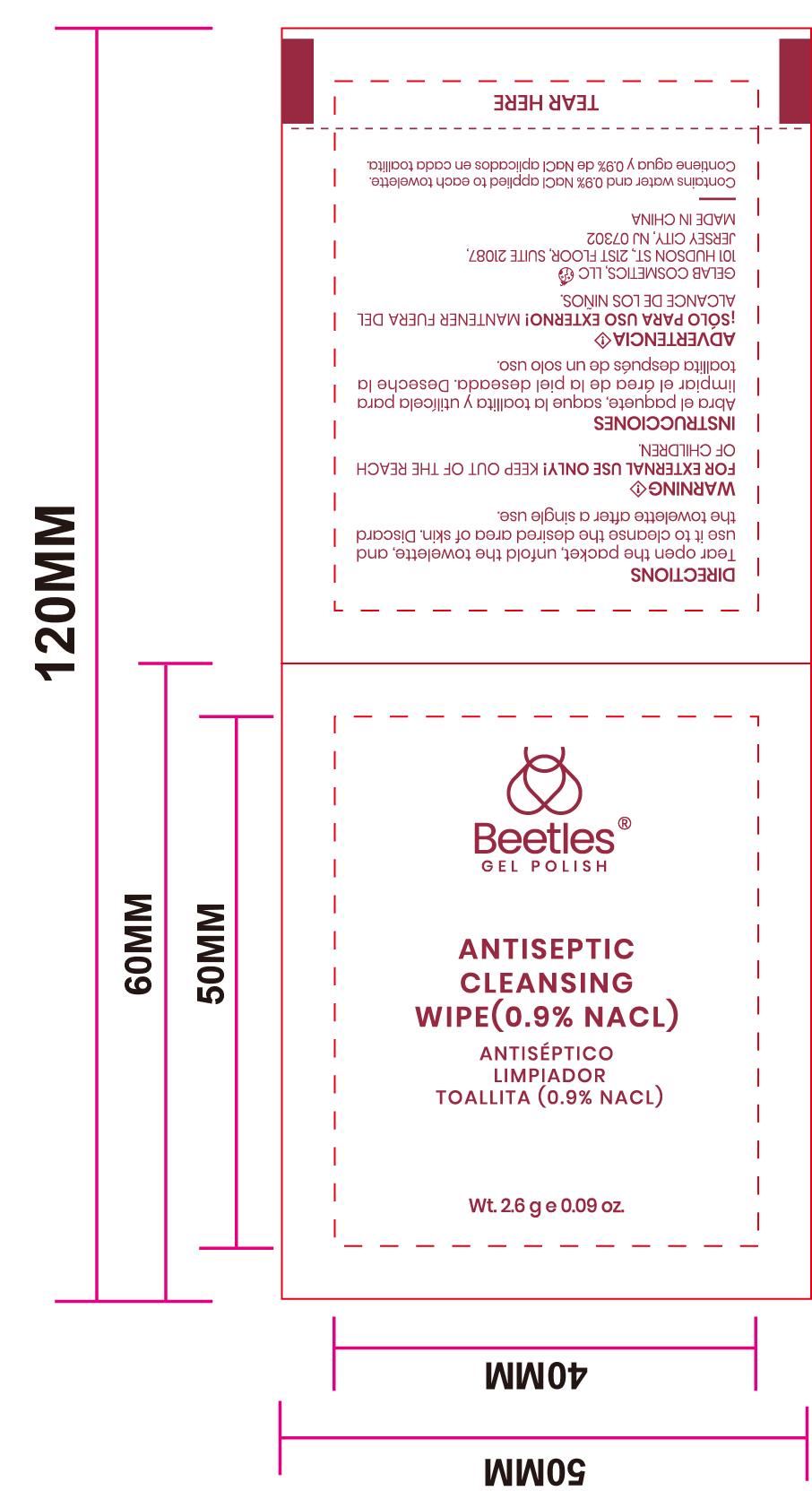 DRUG LABEL: ANTISEPTIC CLEANSING WIPE(0.9% NACL)
NDC: 84449-006 | Form: PATCH
Manufacturer: SHENZHEN BENLIJU BIO-TECH CO.,LTD
Category: otc | Type: HUMAN OTC DRUG LABEL
Date: 20260105

ACTIVE INGREDIENTS: PHENOXYETHANOL 0.01 g/1.5 g
INACTIVE INGREDIENTS: SODIUM CHLORIDE 0.02 g/1.5 g; WATER 1.47 g/1.5 g

ACTIVE INGREDIENT

Phenoxyethanol

PURPOSE

For cleansing the skin in the desired area

INDICATIONS AND USAGE

For cleansing the skin in the desired area

WARNINGS

For external use

DO NOT USE

KEEP OUT OF THE REACH IOF CHILDREN.

When using this product keep out of eyes.

*Stop use if irritation and redness develop. If condition persists consult your health care practioner.

*Stop use and ask a doctor if irritation or rash occurs. These may be signs of a serious condition.

KEEP OUT OF THE REACH IOF CHILDREN.

DOSAGE AND ADMINISTRATION

Tear open the packet, unfold the towelette. and、use it to cleanse the desired area of skin. Discardthe towelette after a single use.

STORAGE AND HANDLING

Store at room temperature.

INACTIVE INGREDIENT

Sodium chloride, Deionized water